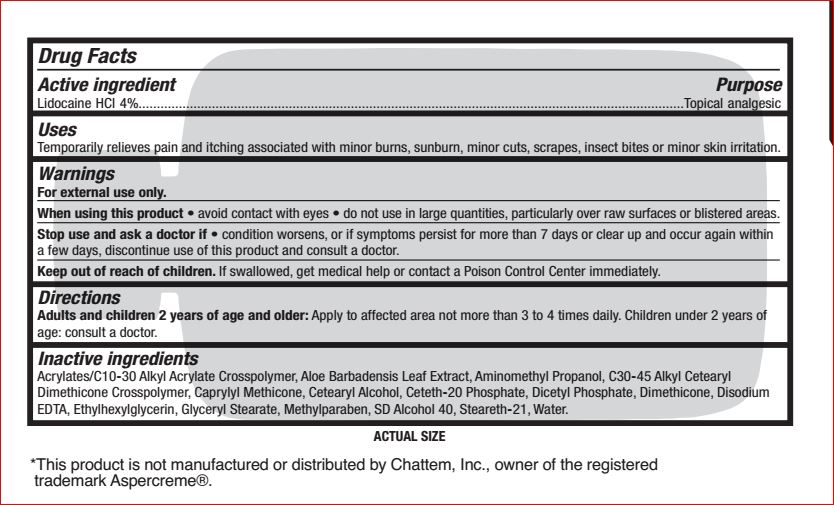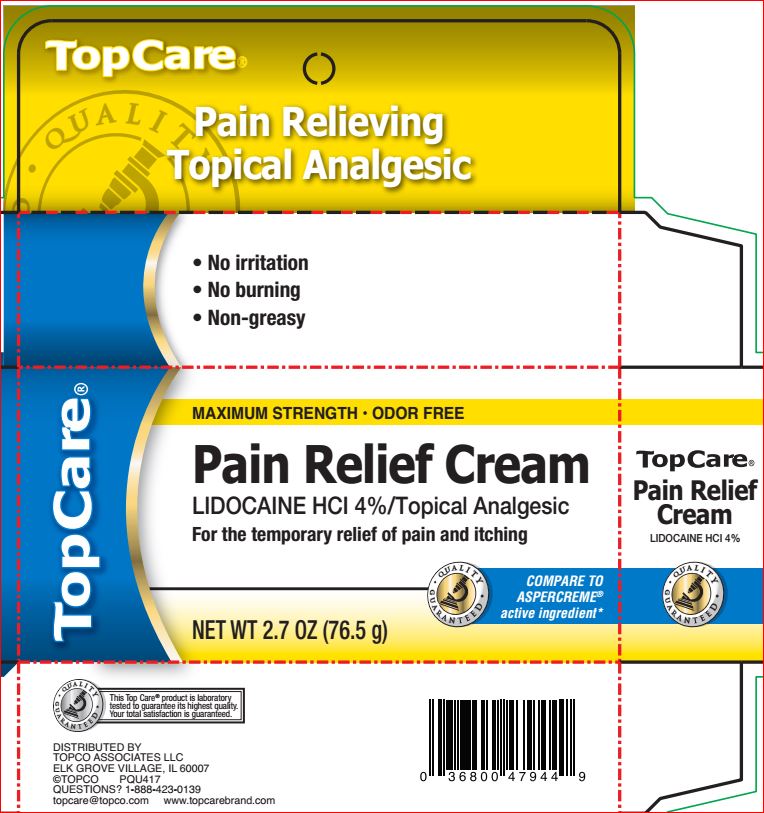 DRUG LABEL: Pain Relief
NDC: 36800-740 | Form: CREAM
Manufacturer: Topco
Category: otc | Type: HUMAN OTC DRUG LABEL
Date: 20180725

ACTIVE INGREDIENTS: LIDOCAINE HYDROCHLORIDE 4 g/100 g
INACTIVE INGREDIENTS: ALOE VERA LEAF; AMINOMETHYLPROPANOL; CAPRYLYL TRISILOXANE; CETOSTEARYL ALCOHOL; Ceteth-20 Phosphate; DIHEXADECYL PHOSPHATE; Dimethicone; EDETATE DISODIUM; Ethylhexylglycerin; GLYCERYL MONOSTEARATE; Methylparaben; ALCOHOL; Steareth-21; Water

Drug Facts

Active ingredient Purpose

Lidocaine HCl 4% Topical Analgesic

Uses

Uses For temporary relief of pain and itching associated with minor burns, sunburn, minor cuts, scrapes, insect bites or minor skin irritation

Warnings

For external use only

When using this product • avoid contact with eyes • do not use in large quantities, particularly over raw surfaces or blistered areas.

Stop use and ask a doctor if • condition worsens • symptoms last more than 7 days or clear up and occur again within a few days

Keep out of reach of the children.

If product is swallowed, get medical help or contact a Poison Control Center right away

Directions

Adults and children 2 years of age and older: Apply to affected area not more than 3 to 4 times daily. Children under 2 years of age: consult a doctor.

Inactive ingredients

Acrylates/C10-30 Alkyl Acrylate Crosspolymer, Aloe Barbadensis Leaf Extract, Aminomethyl Propanol, C30-45 Alkyl Cetearyl Dimethicone, Crosspolymer, Caprylyl Methicone, Cetearyl Alcohol, Ceteth-20 Phosphate, Dicetyl Phosphate, Dimethicone, Disodium EDTA, Ethylhexylglycerin, Glyceryl Stearate, Methylparaben, SD Alcohol 40, Steareth-21, Water